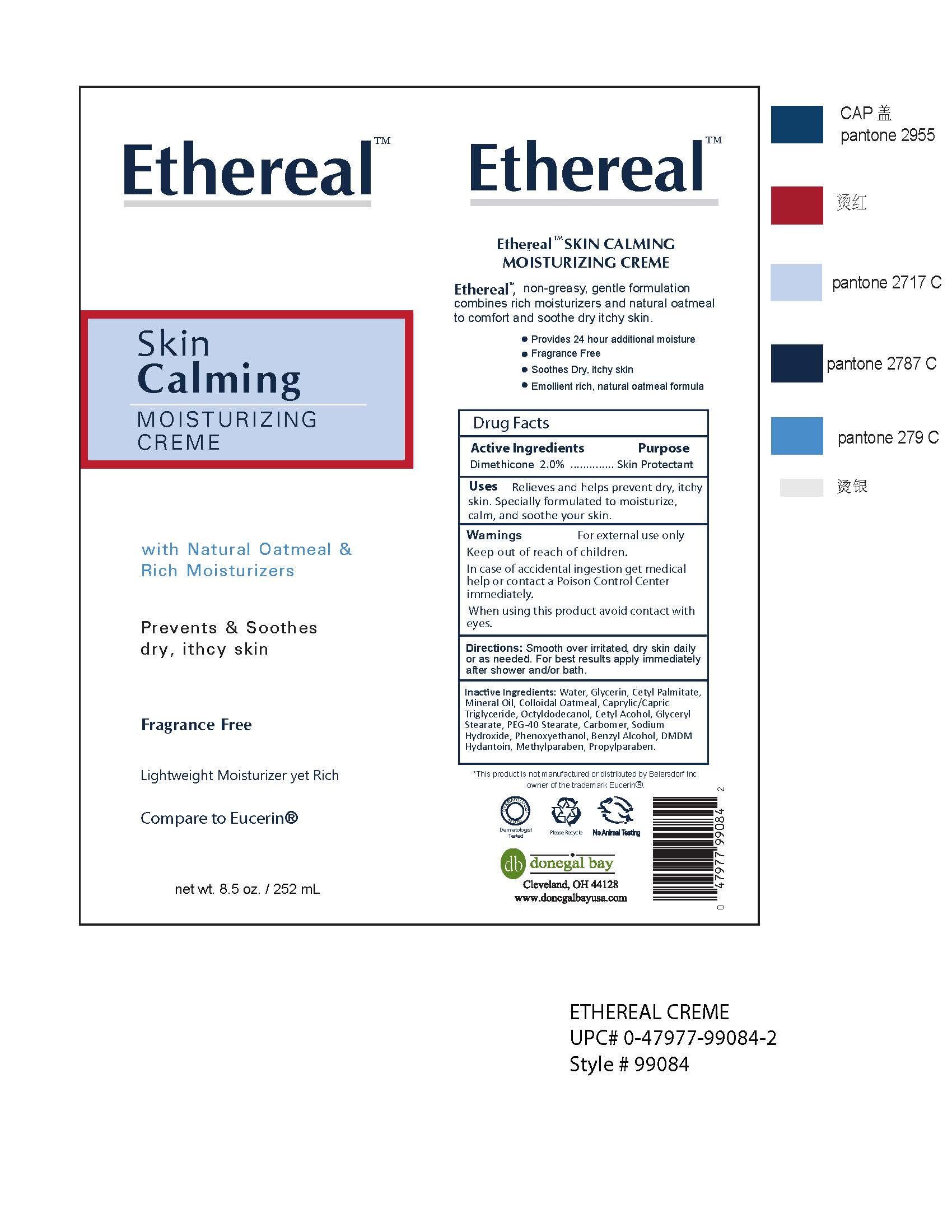 DRUG LABEL: Ethereal Skin Calming Moisturizing Cream
NDC: 70990-003 | Form: CREAM
Manufacturer: Donegal Bay Ltd
Category: otc | Type: HUMAN OTC DRUG LABEL
Date: 20161012

ACTIVE INGREDIENTS: DIMETHICONE 2 g/100 mL
INACTIVE INGREDIENTS: WATER; GLYCERIN; CETYL PALMITATE; MINERAL OIL; CAPRYLIC/CAPRIC/LAURIC TRIGLYCERIDE; OCTYLDODECANOL; CETYL ALCOHOL; GLYCERYL STEARATE SE; PEG-40 STEARATE; CARBOMER COPOLYMER TYPE A; SODIUM HYDROXIDE; PHENOXYETHANOL; BENZYL ALCOHOL; METHYLPARABEN; PROPYLPARABEN; DMDM HYDANTOIN

Daily Moisturizing Lotion

Active Ingredient:

Dimethicone 2.0%

Purpose:

Skin Protectant

Uses:

Relieves and helps prevent dry, itchy skin. Specially formulated to moisturize, calm, and soothe your skin.

Warnings:

For external use only

When using this product, avoid contacting with eyes

STOP USE

In case of accidental ingestion get medical help or contact a Poison Control Center immediately.

Keep out of reach of children.

DOSAGE AND ADMINISTRATION

Direction:

Smooth over irritated, dry skin daily or as needed. For best results apply immediately after shower or/and bath.

Inactive Ingredients:

Water, Glycerin, Cetyl Palmitate, Mineral Oil, Colloidal Oatmeal, Caprylic/Capric Triglyceride, Octyldodecanol, Cetyl Alcohol, Glyceryl Stearate, PEG-40 Stearate, Carbomer, Sodium Hydroxide, Phenoxyethanol, Benzyl Alcohol, Methylparaben, Propylparaben, DMDM Hydantoin